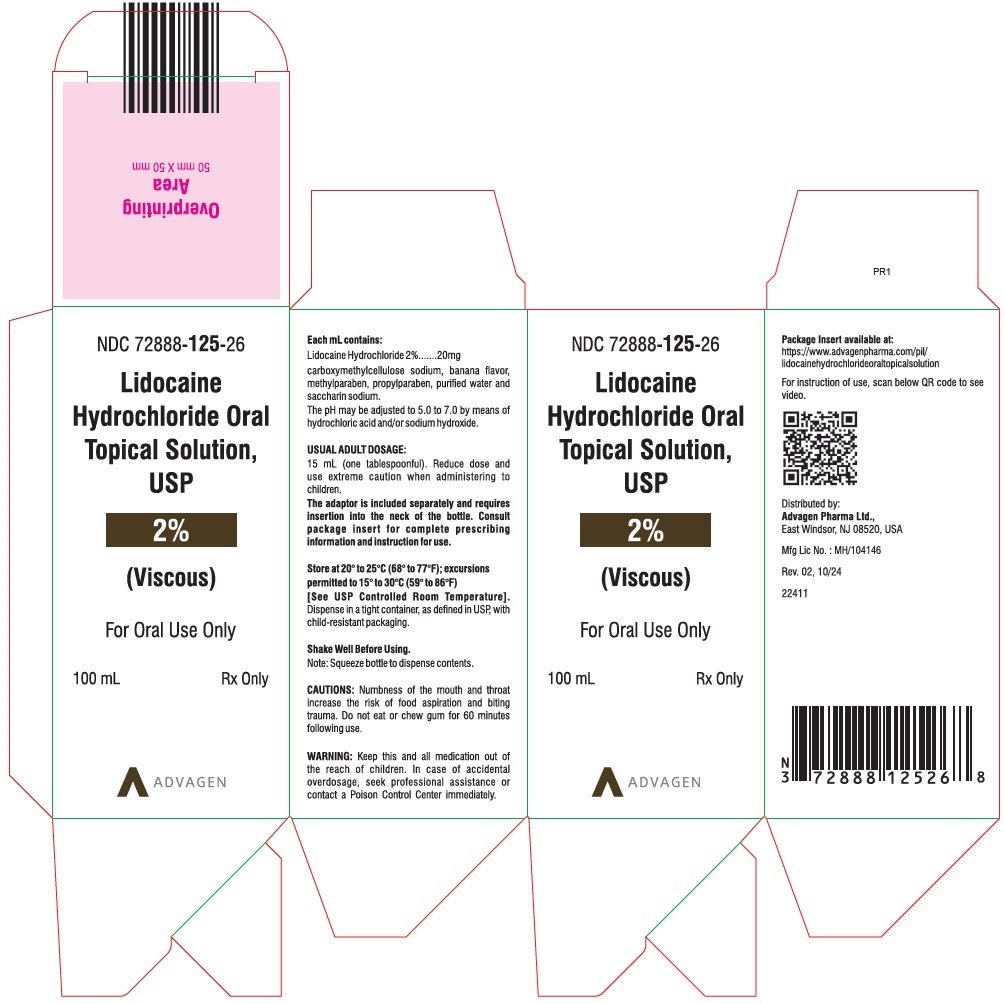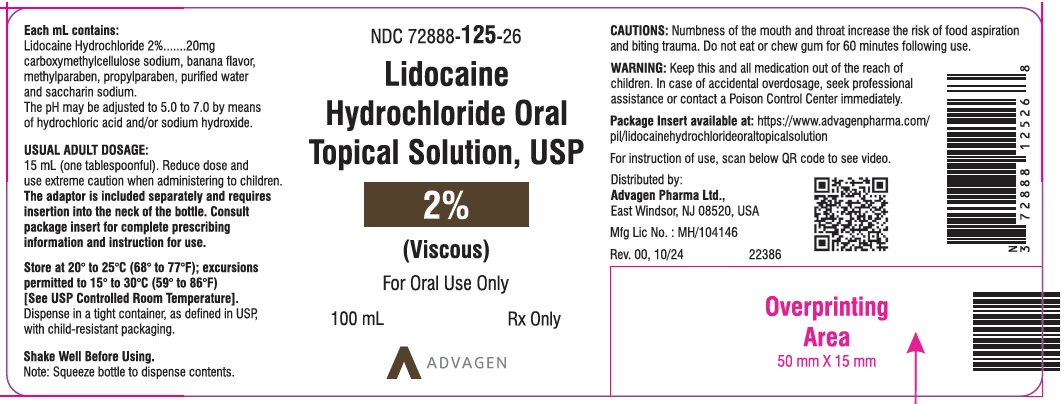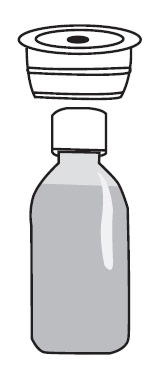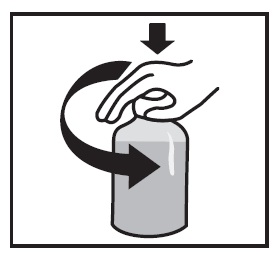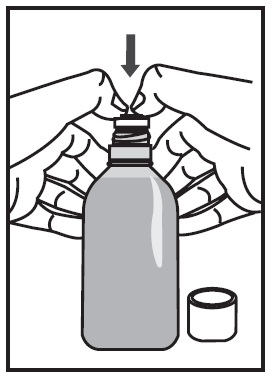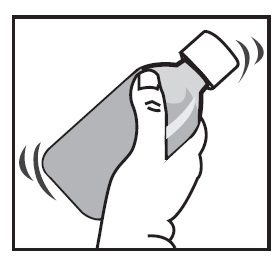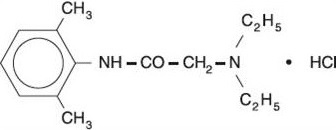 DRUG LABEL: Lidocaine hydrochloride
NDC: 72888-125 | Form: SOLUTION
Manufacturer: Advagen Pharma Ltd
Category: prescription | Type: HUMAN PRESCRIPTION DRUG LABEL
Date: 20260218

ACTIVE INGREDIENTS: LIDOCAINE HYDROCHLORIDE 20 mg/1 mL
INACTIVE INGREDIENTS: CARBOXYMETHYLCELLULOSE SODIUM, UNSPECIFIED; METHYLPARABEN; PROPYLPARABEN; SACCHARIN SODIUM; WATER; HYDROCHLORIC ACID; SODIUM HYDROXIDE

Lidocaine Hydrochloride Oral Topical Solution USP, 2% (Viscous)

A Topical Anesthetic for the Mucous Membranes of the Mouth and Pharynx.

For Oral Use Only

BOXED WARNING

WARNING: Life-threatening and fatal events in infants and young children

Postmarketing cases of seizures, cardiopulmonary arrest, and death in patients under the age of 3 years have been reported with use of Lidocaine Hydrochloride Oral Topical Solution 2% (Viscous) when it was not administered in strict adherence to the dosing and administration recommendations. In the setting of teething pain, Lidocaine Hydrochloride Oral Topical Solution 2% (Viscous) should generally not be used. For other conditions, the use of the product in patients less than 3 years of age should be limited to those situations where safer alternatives are not available or have been tried but failed.

To decrease the risk of serious adverse events with use of Lidocaine Hydrochloride Oral Topical Solution 2% (Viscous), instruct caregivers to strictly adhere to the prescribed dose and frequency of administration and store the prescription bottle safely out of reach of children.

DESCRIPTION

Lidocaine Hydrochloride Oral Topical Solution USP, 2% (Viscous) contains a local anesthetic agent and is administered topically. Lidocaine Hydrochloride Oral Topical Solution USP, 2% (Viscous) contains lidocaine hydrochloride, which is chemically designated as acetamide, 2-(diethylamino)-N-(2,6-dimethylphenyl)-, monohydrochloride and has the following structural formula:

The molecular formula of lidocaine is C14H22N2O. The molecular weight is 234.34.

COMPOSITION OF SOLUTION

Each mL contains 20 mg of lidocaine hydrochloride and following inactive ingredients: banana flavor NAT WONF, carboxymethylcellulose sodium, methylparaben, propylparaben, saccharin sodium and purified water. The pH is adjusted to 5.0 to 7.0 by means of hydrochloric acid and/or sodium hydroxide.

CLINICAL PHARMACOLOGY

Mechanism of Action:

Lidocaine stabilizes the neuronal membrane by inhibiting the ionic fluxes required for the initiation and conduction of impulses, thereby effecting local anesthetic action.

Hemodynamics:

Excessive blood levels may cause changes in cardiac output, total peripheral resistance, and mean arterial pressure. These changes may be attributable to a direct depressant effect of the local anesthetic agent on various components of the cardiovascular system. The net effect is normally a modest hypotension when the recommended dosages are not exceeded.

Pharmacokinetics and Metabolism:

Lidocaine is absorbed following topical administration to mucous membranes, its rate and extent of absorption being dependent upon concentration and total dose administered, the specific site of application, and duration of exposure. In general, the rate of absorption of local anestheticagents following topical application occurs most rapidly after intratracheal administration.

Lidocaine is also well-absorbed from the gastrointestinal tract, but little intact drug appears inthe circulation because of biotransformation in the liver. The plasma binding of lidocaine is dependent on drug concentration, and the fraction bound decreases with increasing concentration. At concentrations of 1 to 4 mcg of free base per mL, 60 to 80 percent of lidocaine is protein bound. Binding is also dependent on the plasma concentration of the alpha-1-acid glycoprotein.

Lidocaine crosses the blood-brain and placental barriers, presumably by passive diffusion.

Lidocaine is metabolized rapidly by the liver, and metabolites and unchanged drug are excreted by the kidneys. Biotransformation includes oxidative N-dealkylation, ring hydroxylation, cleavage of the amide linkage, and conjugation. N-dealkylation, a major pathway of biotransformation, yields the metabolites monoethylglycinexylidide and glycinexylidide. The pharmacological/toxicological actions of these metabolites are similar to, but less potent than, those of lidocaine. Approximately 90% of lidocaine administered is excreted in the form of various metabolites, and less than 10% is excreted unchanged. The primary metabolite in urine is a conjugate of 4-hydroxy-2, 6-dimethylaniline.

The elimination half-life of lidocaine following an intravenous bolus injection is typically 1.5 to 2 hours. Because of the rapid rate at which lidocaine is metabolized, any condition that affects liver function may alter lidocaine kinetics. The half-life may be prolonged two-fold or more in patients with liver dysfunction. Renal dysfunction does not affect lidocaine kinetics but may increase the accumulation of metabolites.

Factors such as acidosis and the use of CNS stimulants and depressants affect the CNS levels of lidocaine required to produce overt systemic effects. Objective adverse manifestations become increasingly apparent with increasing venous plasma levels above 6.0 mcg free baseper mL. In the rhesus monkey arterial blood levels of 18 to 21 mcg/mL have been shown to be threshold for convulsive activity.

INDICATIONS AND USAGE

Lidocaine Hydrochloride Oral Topical Solution 2% (Viscous) is indicated for the production of topical anesthesia of irritated or inflamed mucous membranes of the mouth and pharynx. It is also useful for reducing gagging during the taking of X-ray pictures and dental impressions.

CONTRAINDICATIONS

Lidocaine is contraindicated in patients with a known history of hypersensitivity to local anesthetics of the amide type, or to other components of the solution.

WARNINGS

EXCESSIVE DOSAGE, OR SHORT INTERVALS BETWEEN DOSES, CAN RESULT IN HIGH PLASMA LEVELS AND SERIOUS ADVERSE EFFECTS. PATIENTS SHOULD BE INSTRUCTED TO STRICTLY ADHERE TO THE RECOMMENDED DOSAGE AND ADMINISTRATION GUIDELINES AS SET FORTH IN THIS PACKAGE INSERT.

THE MANAGEMENT OF SERIOUS ADVERSE REACTIONS MAY REQUIRE THE USE OF RESUSCITATIVE EQUIPMENT, OXYGEN, AND OTHER RESUSCITATIVE DRUGS.

Lidocaine should be used with extreme caution if the mucosa in the area of application has been traumatized, since under such conditions there is the potential for rapid systemic absorption.

Life-threatening and fatal events in infants and young children

Postmarketing cases of seizures, cardiopulmonary arrest, and death in patients under the age of 3 years have been reported with use of Lidocaine Hydrochloride Oral Topical Solution 2% (Viscous) when it was not administered in strict adherence to the dosing and administration recommendations. In the setting of teething pain, Lidocaine Hydrochloride Oral Topical Solution 2% (Viscous) should generally not be used. For other conditions, the use of the product in patients less than 3 years of age should be limited to those situations where safer alternatives are not available or have been tried but failed.

Methemoglobinemia

Cases of methemoglobinemia have been reported in association with local anesthetic use. Although all patients are at risk for methemoglobinemia, patients with glucose-6-phosphate dehydrogenase deficiency, congenital or idiopathic methemoglobinemia, cardiac or pulmonary compromise, infants under 6 months of age, and concurrent exposure to oxidizing agents or their metabolites are more susceptible to developing clinical manifestations of the condition. If local anesthetics must be used in these patients, close monitoring for symptoms and signs of methemoglobinemia is recommended.

Signs of methemoglobinemia may occur immediately or may be delayed some hours after exposure, and are characterized by a cyanotic skin discoloration and/or abnormal coloration of the blood.
Methemoglobin levels may continue to rise; therefore, immediate treatment is required to avert more serious central nervous system and cardiovascular adverse effects, including seizures, coma, arrhythmias, and death. Discontinue Lidocaine Hydrochloride Oral Topical Solution 2% (Viscous) and any other oxidizing agents. Depending on the severity of the signs and symptoms, patients may respond to supportive care, i.e., oxygen therapy, hydration. A more severe clinical presentation may require treatment with methylene blue, exchange transfusion, or hyperbaric oxygen.

PRECAUTIONS

Information for Patients:

Parents and caregivers should be cautioned about the following:

- For patients under 3 years of age, special care must be given to accurately measuring the prescribed dose and not administering the product more often than prescribed.
- To ensure accuracy, we recommend you use a measuring device to carefully measure the correct volume.
- The product should only be used for the prescribed indication.
- To reduce the risk of accidental ingestion, the product container should be tightly closed and the product should be stored well out of reach of all children immediately after each use.
- If the patient shows signs of systemic toxicity (e.g., lethargy, shallow breathing, seizure activity) emergency medical attention should be sought immediately and no additional product should be administered.
- Unused product should be discarded in a manner that prevents possible exposureto children andpets.

All patients should be aware that when topical anesthetics are used in the mouth or throat, the production of topical anesthesia may impair swallowing and thus enhance the danger of aspiration. For this reason, food should not be ingested for 60 minutes following use of local anesthetic preparations in the mouth or throat area. This is particularly important in children because of their frequency of eating.

Numbness of the tongue or buccal mucosa may increase the danger of biting trauma. For this reason food and/or chewing gum should not be used while the mouth or throat area is anesthetized.

Inform patients that use of local anesthetics may cause methemoglobinemia, a serious condition that must be treated promptly. Advise patients or caregivers to seek immediate medical attention if they or someone in their care experience the following signs or symptoms: pale, gray, or blue colored skin (cyanosis); headache; rapid heart rate; shortness of breath; lightheadedness; or fatigue".

General:

The safety and effectiveness of lidocaine depend on proper dosage, correct technique, adequate precautions, and readiness for emergencies (see WARNINGSand ADVERSE REACTIONS). The lowest dosage that results in effective anesthesia should be used to avoid high plasma levels and serious adverse effects. Repeated doses of lidocaine may cause significant increases in blood levels with each repeated dose because of slow accumulation of the drug and/or its metabolites. Tolerance varies with the status of the patient. Debilitated, elderly patients, acutely ill patients, and children should be given reduced doses commensurate with their age, weight and physical condition. Lidocaine should also be used with caution in patients with severe shock or heart block.

Lidocaine Hydrochloride Oral Topical Solution 2% (Viscous) should be used with caution in persons with known drug sensitivities. Patients allergic to paraaminobenzoic acid derivatives (procaine, tetracaine, benzocaine, etc.) have not shown cross sensitivity to lidocaine.

Drug Interactions:

Patients who are administered local anesthetics are at increased risk of developing methemoglobinemia when concurrently exposed to the following drugs, which could include other local anesthetics:

Examples of Drugs Associated with Methemoglobinemia:

Class | Examples
Nitrates/Nitrites | nitric oxide, nitroglycerin, nitroprusside, nitrous oxide
Local anesthetics | articaine, benzocaine, bupivacaine, lidocaine, mepivacaine, prilocaine, procaine, ropivacaine, tetracaine
Antineoplastic agents | cyclophosphamide, flutamide, hydroxyurea, ifosfamide, rasburicase
Antibiotics | dapsone, nitrofurantoin, para-aminosalicylic acid, sulfonamides
Antimalarials | chloroquine, primaquine
Anticonvulsants | phenobarbital, phenytoin, sodium valproate
Other drugs | acetaminophen, metoclopramide, quinine, sulfasalazine

Carcinogenesis, Mutagenesis, Impairment of Fertility:

Studies of lidocaine in animals to evaluate the carcinogenic and mutagenic potential or the effect on fertility have not been conducted.

Pregnancy

Teratogenic Effects.

Reproduction studies have been performed in rats at doses up to 6.6 times the human dose and have revealed no evidence of harm to the fetus caused by lidocaine. There are, however, no adequate and well-controlled studies in pregnant women. Because animal reproduction studies are not always predictive of human response, this drug should be used in pregnancy only if clearly needed.

Nursing Mothers:

It is not known whether this drug is excreted in human milk. Because many drugs are excreted in human milk, caution should be exercised when lidocaine is administered to nursing women.

Pediatric Use:

Dosages in children should be reduced, commensurate with age, body weight and physical condition. See DOSAGE AND ADMINISTRATION.

ADVERSE REACTIONS

Adverse experiences following the administration of lidocaine are similar in nature to those observed with other amide local anesthetic agents. These adverse experiences are, in general, dose-related and may result from high plasma levels caused by excessive dosage or rapid absorption, or may result from a hypersensitivity, idiosyncrasy or diminished tolerance on the part of the patient. Serious adverse experiences are generally systemic in nature. The following types are those most commonly reported:

Central Nervous System:

CNS manifestations are excitatory and/or depressant and may be characterized by lightheadedness, nervousness, apprehension, euphoria, confusion, dizziness, drowsiness, tinnitus, blurred or double vision, vomiting, sensations of heat, cold or numbness, twitching, tremors, convulsions, unconsciousness, respiratory depression and arrest. The excitatory manifestations may be very brief or may not occur at all, in which case the first manifestation of toxicity may be drowsiness merging into unconsciousness and respiratory arrest.

Drowsiness following the administration of lidocaine is usually an early sign of a high blood level of the drug and may occur as a consequence of rapid absorption.

Cardiovascular System:

Cardiovascular manifestations are usually depressant and are characterized by bradycardia, hypotension, and cardiovascular collapse, which may lead to cardiac arrest.

Allergic:

Allergic reactions are characterized by cutaneous lesions, urticaria, edema or anaphylactoid reactions. Allergic reactions may occur as a result of sensitivity either to the local anesthetic agent or to the methylparaben and/or propylparaben used in this formulation. Allergic reactions as a result of sensitivity to lidocaine are extremely rare and, if they occur, should be managed by conventional means. The detection of sensitivity by skin testing is of doubtful value.
To report SUSPECTED ADVERSE REACTIONS, contact Advagen Pharma Ltd, at 866-488-0312 or FDA at 1-800- FDA-1088 or www.fda.gov/medwatch.

OVERDOSAGE

Acute emergencies from local anesthetics are generally related to high plasma levels encountered during therapeutic use of local anesthetics (see ADVERSE REACTIONS, WARNINGS, and PRECAUTIONS).

Management of Local Anesthetic Emergencies:

The first consideration is prevention, best accomplished by careful and constant monitoring of cardiovascular and respiratory vital signs and the patient's state of consciousness after each local anesthetic administration.

The first step in the management of convulsions consists of immediate attention to the maintenance of a patent airway and assisted or controlled ventilation with oxygen. In situations where trained personnel are readily available, ventilation should be maintained and oxygen should be delivered by a delivery system capable of permitting immediate positive airway pressure by mask. Immediately after the institution of these ventilatory measures, the adequacy of the circulation should be evaluated, keeping in mind that drugs used to treat convulsions sometimes depress the circulation when administered intravenously. Should convulsions persist despite adequate respiratory support, and if the status of the circulation permits, small increments of an ultra-short acting barbiturate (such as thiopental or thiamylal) or a benzodiazepine (such as diazepam) may be administered intravenously. The clinician should be familiar, prior to use of local anesthetics, with these anticonvulsant drugs. Supportive treatment of circulatory depression may require administration of intravenous fluids and, when appropriate, a vasopressor as indicated by the clinical situation (e.g., ephedrine).

If not treated immediately, both convulsions and cardiovascular depression can result in hypoxia, acidosis, bradycardia, arrhythmias and cardiac arrest. If cardiac arrest should occur, standard cardiopulmonary resuscitative measures should be instituted.

Dialysis is of negligible value in the treatment of acute overdosage with lidocaine.

The oral LD50 of lidocaine in non-fasted female rats is 459 (346 to 773) mg/kg (as the salt) and 214 (159 to 324) mg/kg (as the salt) in fasted female rats.

DOSAGE AND ADMINISTRATION

Adult:

The maximum recommended single dose of Lidocaine Hydrochloride Oral Topical Solution 2% (Viscous) for healthy adults should be such that the dose of lidocaine does not exceed 4.5 mg/kg or 2 mg/lb body weight and does not in any case exceed a total of 300 mg.

For symptomatic treatment of irritated or inflamed mucous membranes of the mouth and pharynx, the usual adult dose is one 15 mL undiluted. For use in the mouth, the solution should be swished around in the mouth and spit out. For use in the pharynx, the undiluted solution should be gargled and may be swallowed. This dose should not be administered at intervals of less than three hours, and not more than eight doses should be given in a 24-hour period. The dosage should be adjusted commensurate with the patient's age, weight and physical condition (see PRECAUTIONS).

Pediatric:

Care must be taken to ensure correct dosage in all pediatric patients as there have been cases of overdose due to inappropriate dosing.

It is difficult to recommend a maximum dose of any drug for children since this varies as a function of age and weight. For children over 3 years of age who have a normal lean body mass and normal body development, the maximum dose is determined by the child's weight or age. For example: in a child of 5 years weighing 50 lbs., the dose of lidocaine hydrochloride should not exceed 75 to 100 mg (3.7 to 5 mL of Lidocaine Hydrochloride Oral Topical Solution 2% Viscous).

For infants and in children under 3 years of age, the solution should be accurately measured and no more than 1.2 mL be applied to the immediate area with a cotton-tipped applicator. Wait at least 3 hours before giving the next dose; a maximum of four doses may be given in a 12-hour period. Lidocaine Hydrochloride Oral Topical Solution 2% (Viscous) should only be used if the underlying condition requires treatment with a volume of product that is less than or equal to 1.2 mL.

HOW SUPPLIED

Lidocaine Hydrochloride Oral Topical Solution USP, 2% (Viscous) is a clear, colorless , viscous solution supplied in 100 mL low density polyethylene squeeze bottles. Supplied with press-in bottle adapter.

NDC 72888-125-26

Store at 20º to 25ºC (68º to 77ºF); excursions permitted to 15° to 30°C (59° to 86°F) [See USP Controlled Room Temperature].

SHAKE WELL BEFORE USE.

Distributed by:
Advagen Pharma Ltd.,
East Windsor, NJ 08520, USA

Revised: 00, 10/2024

INSTRUCTIONS FOR USE

Lidocaine Hydrochloride Oral Topical Solution, USP

Each ml contains 2% Lidocaine

Instructions for Use

Read these instructions carefully to learn how to use the medicine

dispensing system correctly.

The Medicine Dispensing System

There are 2 parts to the dispensing system:

1. A plastic adapterthat you push into the neck of the bottle the first time that you open the bottle. The adapter must always stay in the bottle.
2. A bottle containing the medicine with a child resistant cap. Always replace the cap after use.

Preparing the Bottle

1. Remove the child-resistant cap by pushing it firmly down and turning it counterclockwise - to the left (as shown on the top of the cap).

Note:Save the cap so you can close the bottle after each use.

1. Hold the open bottle upright on a table and push the plastic adapter firmlyinto the neck of the bottle as far as you can.

1. Replace the cap to be sure that the adapter has been fully forced into the neck of the bottle.

Note:You may not be able to push the adapter fully down, but it will be forced into the bottle when you screw the cap back on.

The adapter must always stay in the bottle. The child-resistant cap should seal the bottle in between use.

Taking the Medicine

1. Shake the bottle well. Prepare the dose right away.
2. Push and turn the child-resistant cap to open the bottle.

Note:Always replace the cap after use.

1. Squeeze bottle to dispense contents.
2. Replace the child-resistant cap after use.

Distributed by:
Advagen Pharma Ltd.,
East Windsor, NJ 08520, USA

Revised: 00, 10/2024

PACKAGE LABEL-PRINCIPAL DISPLAY PANEL

Lidocaine Hydrochloride Oral Topical Solution, USP (Viscous) 2% - NDC 72888-125-26 -100 mL Bottle Label

Lidocaine Hydrochloride Oral Topical Solution, USP (Viscous) 2% - NDC 72888-125-26 -100 mL Carton Label